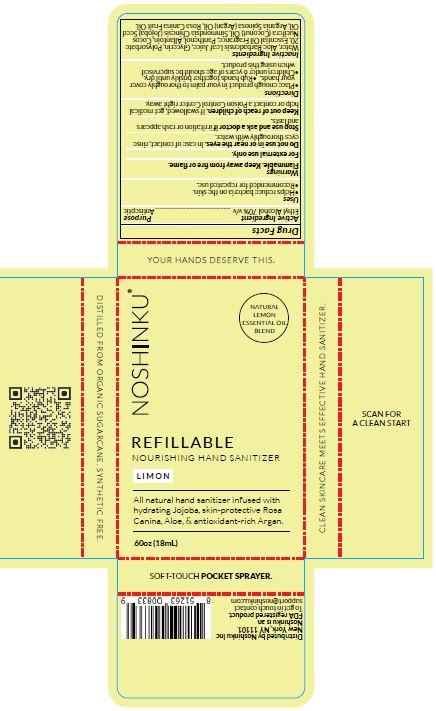 DRUG LABEL: Nourishing Hand Sanitizer
NDC: 73898-006 | Form: SOLUTION
Manufacturer: Noshinku
Category: otc | Type: HUMAN OTC DRUG LABEL
Date: 20240515

ACTIVE INGREDIENTS: ALCOHOL 70 mL/100 mL
INACTIVE INGREDIENTS: POLYSORBATE 20; ALOE VERA LEAF; ALLANTOIN; COCONUT OIL; JOJOBA OIL; ARGAN OIL; ROSA CANINA FRUIT OIL; PANTHENOL; WATER; GLYCERIN

Noshinku Limon Hand Sanitizer (73898-006)

ACTIVE INGREDIENT

ETHYL ALCOHOL 70% v/v

PURPOSE

ANTISEPTIC

USES

- HELPS REDUCE BACTERIA ON THE SKIN.
- RECOMMENDED FOR REPEATED USE.

WARNINGS

FLAMMABLE. KEEP AWAY FROM FIRE OR FLAME.

FOR EXTERNAL USE ONLY.

DO NOT USE IN OR NEAR THE EYES. IN CASE OF CONTACT, RINSE EYES THOROUGHLY WITH WATER.

STOP USE AND ASK A DOCTOR IF IRRITATION OR RASH APPEARS AND LASTS.

KEEP OUT OF REACH OF CHILDREN. IF SWALLOWED, GET MEDICAL HELP OR CONTACT POISON CONTROL CENTER RIGHT AWAY.

DIRECTIONS

- Place enough product in your palm to thoroughly cover your hands.
- Rub hands together briskly until dry.
- Children under 6 years of age should be supervised when using this product.

INACTIVE INGREDIENTS

Water, Aloe Barbadensis Leaf Juice, Glycerin, Polysorbate 20, Essential Oil Fragrance, Panthenol, Allantoin, Cocos Nucifera (Coconut) Oil, Simmondsia Chinesis (Jojoba) Seed Oil, Argania Spinosa (Argan) Oil, Rosa Canina Fruit Oil.